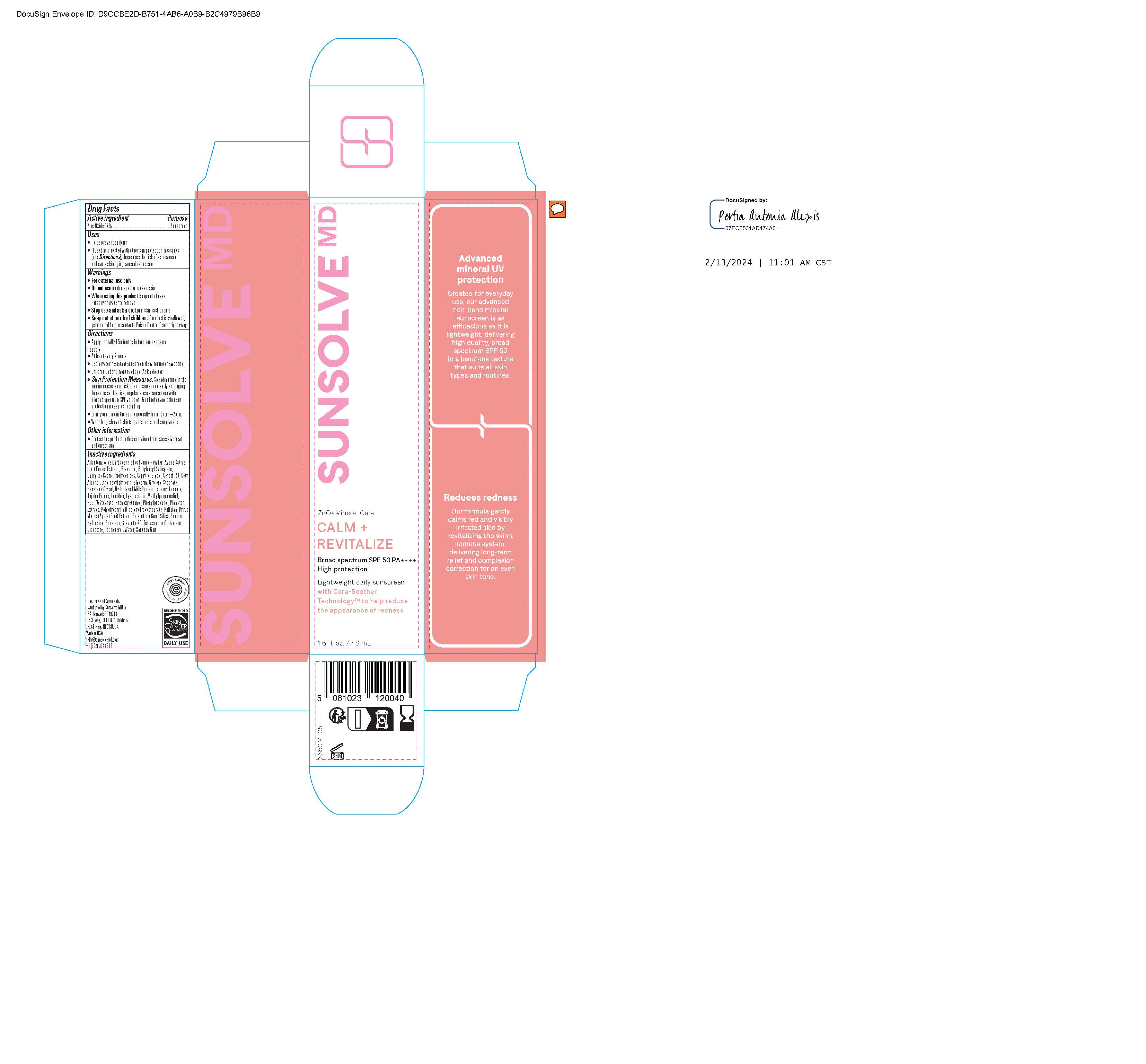 DRUG LABEL: Sunsolve MD Calm and Revitalize
NDC: 84878-654 | Form: LOTION
Manufacturer: Sunsolve MD Inc
Category: otc | Type: HUMAN OTC DRUG LABEL
Date: 20251114

ACTIVE INGREDIENTS: ZINC OXIDE 132 mg/1 mL
INACTIVE INGREDIENTS: LECITHIN, SOYBEAN; POLYGLYCERYL-2 DIPOLYHYDROXYSTEARATE; HYDROLYZED JOJOBA ESTERS (ACID FORM); METHYLPROPANEDIOL; CAPRYLYL GLYCOL; PHENYLPROPANOL; XANTHAN GUM; ISOAMYL LAURATE; HEXYLENE GLYCOL; TOCOPHEROL; CETYL ALCOHOL; ETHYLHEXYLGLYCERIN; GLYCERIN; SILICON DIOXIDE; WATER; .ALPHA.-BISABOLOL, (+)-; BUTYLOCTYL SALICYLATE; CETETH-20; PULLULAN; SQUALANE; STEARETH-20; CAPRYLIC/CAPRIC TRIGLYCERIDE; TETRASODIUM GLUTAMATE DIACETATE; PHENOXYETHANOL; ALLANTOIN; PEG-75 STEARATE; GLYCERYL STEARATE; SCLEROTIUM GUM; AVENA SATIVA (OAT) KERNEL OIL; ALOE BARBADENSIS LEAF JUICE; SODIUM HYDROXIDE; PYRUS MALUS (APPLE) FRUIT

Sunsolve MD Calm and Revitalize